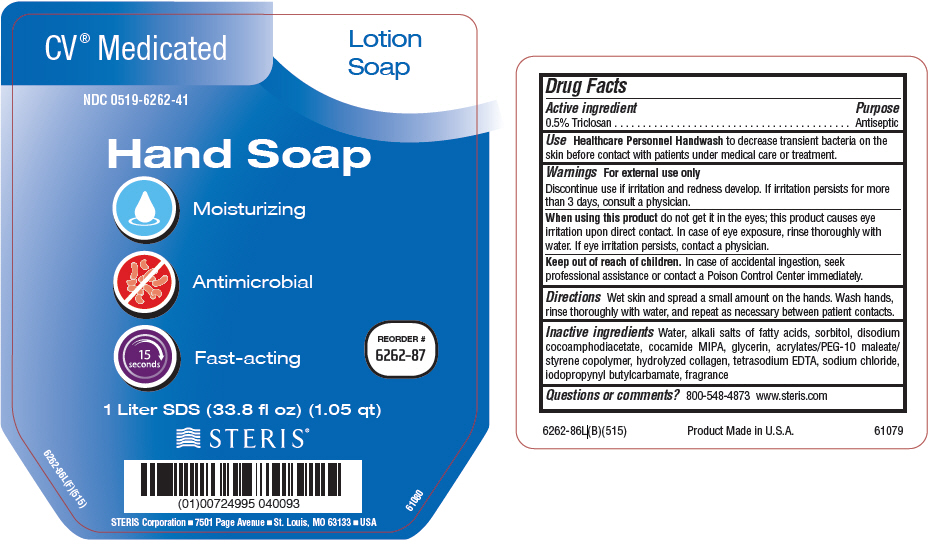 DRUG LABEL: CV Medicated
NDC: 0519-6262 | Form: SOAP
Manufacturer: STERIS Corporation
Category: otc | Type: HUMAN OTC DRUG LABEL
Date: 20150529

ACTIVE INGREDIENTS: TRICLOSAN 0.5 g/100 mL
INACTIVE INGREDIENTS: WATER; SORBITOL; DISODIUM COCOAMPHODIACETATE; COCO MONOISOPROPANOLAMIDE; GLYCERIN; EDETATE SODIUM; METHACRYLATE/METHOXY PEG-10 MALEATE/STYRENE COPOLYMER; GELATIN HYDROLYSATE (PORCINE SKIN, MW 3000); SODIUM CHLORIDE; IODOPROPYNYL BUTYLCARBAMATE

CV® Medicated Lotion Soap

Drug Facts

Active ingredient

0.5% Triclosan

Purpose

Antiseptic

Use

Healthcare Personnel Handwash to decrease transient bacteria on the skin before contact with patients under medical care or treatment.

Warnings

For external use only

STOP USE

Discontinue use if irritation and redness develop. If irritation persists for more than 3 days, consult a physician.

When using this product do not get it in the eyes; this product causes eye irritation upon direct contact. In case of eye exposure, rinse thoroughly with water. If eye irritation persists, contact a physician.

Keep out of reach of children. In case of accidental ingestion, seek professional assistance or contact a Poison Control Center immediately.

Directions

Wet skin and spread a small amount on the hands. Wash hands, rinse thoroughly with water, and repeat as necessary between patient contacts.

Inactive ingredients

Water, alkali salts of fatty acids, sorbitol, disodium cocoamphodiacetate, cocoamide DEA, glycerin, acrylates/PEG-10 maleate/styrene copolymer, hydrolyzed collagen, tetrasodium EDTA, sodium chloride, iodopropynyl butylcarbamate, fragrance

Questions or comments?

800-548-4873 www.steris.com

PRINCIPAL DISPLAY PANEL - 1 Liter Bottle Label

CV® Medicated

Lotion
Soap

NDC 0519-6262-41

Hand Soap

Moisturizing

Antimicrobial

15
seconds
Fast-acting

REORDER #
6262-87

1 Liter SDS (33.8 fl oz) (1.05 qt)

STERIS®

STERIS Corporation ■7501 Page Avenue ■ St. Louis, MO 63133 ■ USA

6262-86L(F)(515)

61080